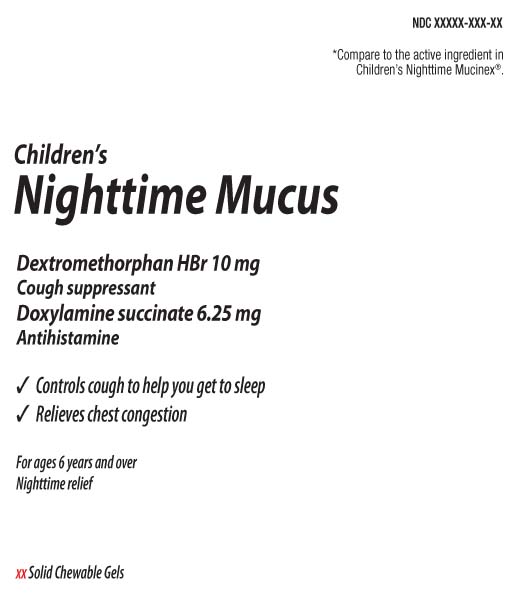 DRUG LABEL: Childrens Nighttime Mucus
NDC: 0363-9360 | Form: CHEWABLE GEL
Manufacturer: Walgreens
Category: otc | Type: HUMAN OTC DRUG LABEL
Date: 20260212

ACTIVE INGREDIENTS: DEXTROMETHORPHAN HYDROBROMIDE 10 mg/1 1; DOXYLAMINE SUCCINATE 6.25 mg/1 1
INACTIVE INGREDIENTS: ANHYDROUS CITRIC ACID; CORN SYRUP; WATER; SUCRALOSE; SUCROSE; FD&C RED NO. 40; TRISODIUM CITRATE DIHYDRATE; ALCOHOL; FD&C BLUE NO. 1; AMMONIUM GLYCYRRHIZATE; GLYCERIN; GLYCYRRHIZIN; MALIC ACID; MALTODEXTRIN; PECTIN; PROPYLENE GLYCOL

Drug Facts

Active ingredients (in each chewable gel)

Dextromethorphan HBr 10 mg

Doxylamine Succinate 6.25 mg

Purposes

Cough suppressant

Antihistamine

Uses

- temporarily relieves cough due to minor throat and bronchial irritation as may occur with a cold
- controls cough to help you get to sleep
- temporarily relieves these symptoms due to hay fever or other upper respiratory allergies:
  - runny nose
  - sneezing
  - itching of the nose or throat
  - itchy, water eyes

Warnings

Do not use

- to make a child sleepy
- if you are now taking a prescription monoamine oxidase inhibitor (MAOI) (certain drugs for depression, psychiatric or emotional conditions, or Parkinson's disease), or for 2 weeks after stopping the MAOI drug. If you do not know if your prescription drug contains an MAOI, ask a doctor or pharmacist before taking this product.

Ask a doctor before use if the child has

- a sodium-restricted diet
- glaucoma
- cough that occurs with too much phlegm (mucus)
- a breathing problem or chronic cough that lasts or occurs with smoking, asthma, chronic bronchitis or emphysema
- trouble urinating due to enlarged prostate gland

Ask a doctor or pharmacist before use if you are

taking sedatives or tranquilizers

When using this product

- do not exceed recommended dosage
- excitability may occur, especially in children
- marked drowsiness may occur
- avoid alcoholic drinks
- alcohol, sedative, and tranquilizers may increase drowsiness
- be careful when driving a motor vehicle or operating machinery

Stop use and ask a doctor if

cough lasts more than 7 days, comes back, or occurs with fever, rash, or headache that lasts. These could be signs of a serious condition.

If pregnant or breast-feeding,

ask a health professional before use

Keep out of reach of children.

In case of overdose, get medical help or contact a Poison Control Center (1-800-222-1222) right away.

Directions

- take every 4 hours, or as directed by a doctor
- chew thoroughly before swallowing
- adult and children 12 years and over: 2 chewable gels every 4 hours, not to exceed 12 chewable gels in any 24-hour period
- children 6 to under 12 years of age: 1 chewable gels in any 24-perios
- children under 6 years of age: do not use

Other information

- each chewable gel contains: sodium 20 mg
- store between 20-25ºC (68-77ºF). Do not refrigerate

Inactive ingredients

citric acid anhydrous, FD&C red 33, FD&C Blue #1, corn syrup, natural flavors (with other natural flavors), flavors, purified water, sodium citrate, sucralose, sucrose

Questions or comments?

Call 1-877-753-3929 Monday-Friday 9AM-5PM EST

Principal Display Panel

*Compare to the active ingredients in Children's Nighttime Mucinex®.

Children's

Nighttime Mucus

Dextromethorphan HBr 10 mg

Cough suppressant

Doxylamine Succinate 6.25 mg

Antihistmine

- Controls cough to help you get to sleep
- Relieves chest congestion

For ages 6 years and over

Nighttime relief

Solid Chewable Gels

Grape Flavor

*This product is not manufactured or distributed by RB Health (US) LLC, distributor of Children's Nighttime Mucinex®.

TAMPER EVIDENT: DO NOT USE IF PRINTED SAFETY SEAL IS BROKEN OR MISSING.

DISTRIBUTED BY: WALGREEN CO

Package Label

WALGREENS Children's Nighttime Chewable Gel Mixed Berry Flavor